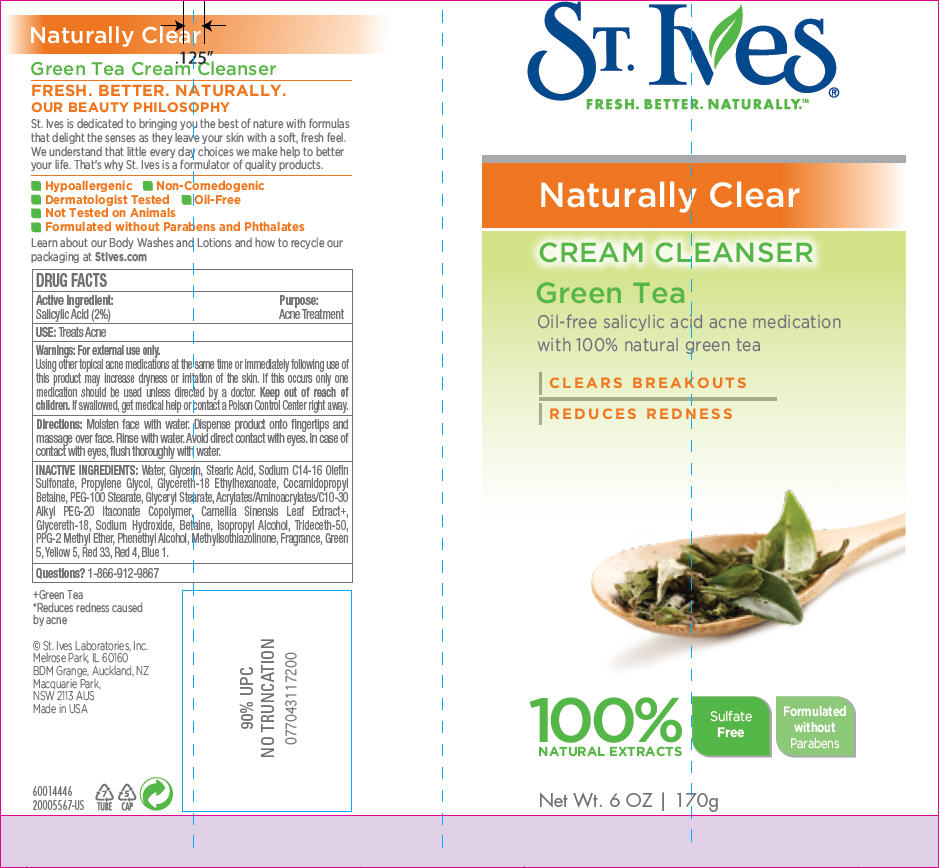 DRUG LABEL: ST. IVES 
NDC: 12488-0700 | Form: SOAP
Manufacturer: Alberto-Culver USA Inc.
Category: otc | Type: HUMAN OTC DRUG LABEL
Date: 20110506

ACTIVE INGREDIENTS: Salicylic Acid 0.02 g/1 g
INACTIVE INGREDIENTS: Water; Glycerin; Stearic Acid; Sodium C14-16 Olefin Sulfonate; Propylene Glycol; Cocamidopropyl Betaine; PEG-100 Stearate; Glyceryl Monostearate; Green Tea Leaf; Sodium Hydroxide; Betaine; Isopropyl Alcohol; Phenylethyl Alcohol; Methylisothiazolinone; D&C Green No. 5; Fd&C Yellow No. 5; D&C Red No. 33; Fd&C Red No. 4; Fd&C Blue No. 1

ST. Ives®
Naturally Clear
CREAM CLEANSER
GREEN TEA

DRUG FACTS

Active Ingredient

Salicylic Acid (2%)

Purpose

Acne Treatment

USE

Treats Acne

Warnings

For external use only.

WHEN USING

Using other topical acne medications at the same time or immediately following use of this product may increase dryness or irritation of the skin. If this occurs only one medication should be used unless directed by a doctor.

Keep out of reach of children. If swallowed, get medical help or contact a Poison Control Center right away.

Directions

Moisten face with water. Dispense product onto fingertips and massage over face. Rinse with water. Avoid direct contact with eyes. In case of contact with eyes, flush thoroughly with water.

INACTIVE INGREDIENTS

Water, Glycerin, Stearic Acid, Sodium C14-16 Olefin Sulfonate, Propylene Glycol, Glycereth-18 Ethylhexanoate, Cocamidopropyl Betaine, PEG-100 Stearate, Glyceryl Stearate, Acrylates/Aminoacrylates/C10-30 Alkyl PEG-20 Itaconate Copolymer, Camellia Sinensis Leaf Extract+, Glycereth-18, Sodium Hydroxide, Betaine, Isopropyl Alcohol, Trideceth-50, PPG-2 Methyl Ether, Phenethyl Alcohol, Methylisothiazolinone, Fragrance, Green 5, Yellow 5, Red 33, Red 4, Blue 1.

Questions?

1-866-912-9867

PRINCIPAL DISPLAY PANEL - 170 g Tube Label

ST. Ives®
FRESH. BETTER. NATURALLY.™

Naturally Clear

CREAM CLEANSER

Green Tea

Oil-free salicylic acid acne medication
with 100% natural green tea

CLEARS BREAKOUTS
REDUCES REDNESS

100%
NATURAL EXTRACTS

Sulfate
Free

Formulated
without
Parabens

Net Wt. 6 OZ | 170g